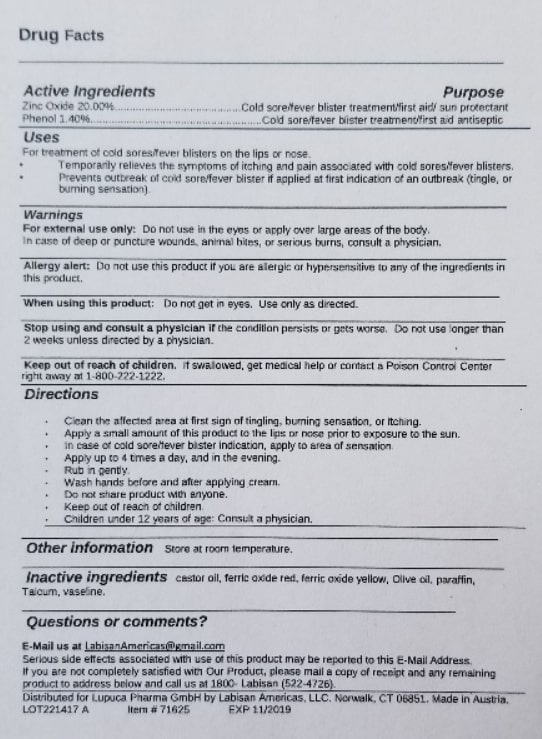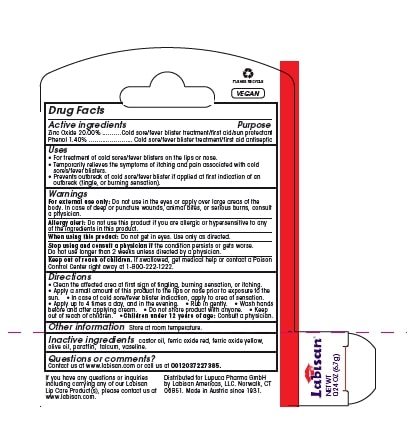 DRUG LABEL: Labisan Cold Sore
NDC: 72941-932 | Form: OINTMENT
Manufacturer: Lupuca Pharma GmbH
Category: otc | Type: HUMAN OTC DRUG LABEL
Date: 20191111

ACTIVE INGREDIENTS: PHENOL 1.4 g/100 g; ZINC OXIDE 20 g/100 g
INACTIVE INGREDIENTS: OLIVE OIL; FERRIC OXIDE RED; CASTOR OIL; TALC; PETROLATUM; MINERAL OIL; FERRIC OXIDE YELLOW

Labisan cold sore/fever blister treatment
Zinc Oxide 20% part347 (suncreen) and 1.4% Phenol (Astringent) (part 310.545(a)(18)(ii).10b, #7- Phenol 0.5 - 1.5% within Monograph,Title 21 active ingredients..

Active Ingredients

Zinc Oxide 20.00%......................................

Phenol 1.40%.....................

Inactive Ingredients

Inactive ingredients: castor oil, ferric oxide red, ferric oxide yellow, olive oil, paraffin, talcum, vaseline.

Keep out of reach Children

Keep out of reach of children. If swallowed, get medical help or contact a Poison Control Center right away at 1-800-222-1222.

Stop using and consult a doctor if the condition persists or gets worse. Do not use longer than 2 weeks unless directed by a doctor.

Stop using and consult a physician if the condition persists or gets worse. Do not use longer than

2 weeks unless directed by a physician.

Warnings

For external use only: Do not use in the eyes, or apply over large areas of the body.

In case of deep or puncture wounds, animal bites, or serious burns, consult a physician.

Stop using and consult a physician if the condition persists or gets worse. Do not use longer than

2 weeks unless directed by a physician.

Directions

Clean the affected area at first sign of tingling, burning sensation, or itching.
Apply a small amount of this product to the lips or nose prior to exposure to the sun.
In case of cold sore/fever blister indication, apply to area of sensation.
Apply up to 4 times a day, and in the evening.
Rub in gently.
Wash hands before and after applying cream.
Do not share product with anyone.
Keep out of reach of children.
Children under 12 years of age: Consult a physician.

Uses

For treatment of cold sores/fever blisters on the lips, face, and/or nose

Temporarily relieves the symptoms of itching and pain associated with cold sores/fever blisters
Prevents outbreak of cold sore/fever blister if applied at first indication of an out break (tingle, or burning sensation)

heals cold sore/fever blisters.

Prevents and heals sun burn to lips and stimulates rapid healing
Full UVA and UVB (Broad Spectrum) Sunburn Prevention.

Precautions Allergy alert. When using product, Stop and consult Physician.

Warnings

For external use only: Do not use in the eyes, or apply over large areas of the body.

In case of deep or puncture wounds, animal bites, or serious burns, consult a physician.

___________________________________________________________________________________________

Allergy alert: Do not use this product if you are allergic or hypersensitive to any of the ingredients in this product.

___________________________________________________________________________________________

When using this product: Do not get in eyes. Use only as directed.

___________________________________________________________________________________________

Stop using and consult a Physician if the condition persists or gets worse. Do not use longer than 2 weeks unless directed by a doctor.

___________________________________________________________________________________________

Keep out of reach of children. If swallowed, get medical help or contact a Poison Control Center right away at 1-800-222-1222.

Indications and Usage

Uses

For treatment of cold sores/fever blisters on the lips or nose.
Temporarily relieves the symptoms of itching and pain associated with cold sores/fever blisters.
Prevents outbreak of cold sore/fever blister if applied at first indication of an outbreak (tingle, or burning sensation).

________________________________________________________________________________

Other information: Store at room temperature.

Do not get in eyes. Use only as directed.

Spanish Version of insert.

Drug Facts

Ingredientes activos y propósito:
Óxido de cinc 20.00% ...... Tratamiento de ampollas febril / úlceras bucales / primeros auxilios / protector solar
Phenol 1.40% .............. Tratamiento de ampolla febril / antiséptico de primeros auxilios
__________________________________________________________________________

Usos
• Para el tratamiento del herpes labial / ampollas en los labios o la nariz.
• Alivia temporalmente los síntomas de picazón y dolor asociado con el herpes labial / ampollas febriles.
• Previene el brote de herpes labial / ampolla febril si se aplica al primer indicio de un brote (cosquilleo o sensación de ardor).
__________________________________________________________________________

Advertencias
Solo para uso externo: no usar en los ojos ni aplicar sobre grandes áreas del cuerpo.
En caso de heridas profundas o punzantes, mordeduras de animales o quemaduras graves, consulte a un médico.
__________________________________________________________________________

Alerta de alergia: No use este producto si es alérgico o hipersensible a cualquiera de los ingredientes de este producto.
__________________________________________________________________________

Al usar este producto: No entrar en los ojos. Utilizar sólo según las indicaciones.
__________________________________________________________________________

Deje de usar y consulte a un médico si la condición persiste o empeora. No lo use por más de 2 semanas a menos que lo indique un médico.
__________________________________________________________________________

Mantener fuera del alcance de los niños. En caso de ingestión, obtenga ayuda médica o comuníquese con un Centro de control de intoxicaciones de inmediato al 1-800-222-1222.
__________________________________________________________________________

Direcciones
• Limpie el área afectada a la primera señal de hormigueo, sensación de ardor o picazón.
• Aplique una pequeña cantidad de este producto en los labios o la nariz antes de exponerse al sol.
• En caso de dolor, herpes labial, fiebre, aplique en el área de la sensación.
• Aplicar hasta 4 veces al día, y por la noche.
• Frote suavemente.
• Lavarse las manos antes y después de aplicar la crema.
• No compartir el producto con nadie.
• Mantener fuera del alcance de los niños.
• Niños menores de 12 años: consultar a un médico.
________________________________________________________________________________

Otra información: Almacenar a temperatura ambiente.
__________________________________________________________________________Ingredientes inactivos: talco, vaselina, , parafina, oleum olivae, oleum ricini, óxido de hierro amarillo y rojo (color).
__________________________________________________________________________

¿Preguntas o comentarios?
Envíenos un correo electrónico a LabisanAmericas@gmail.com
Los efectos secundarios graves asociados con el uso de este producto pueden informarse a esta dirección de correo electrónico.
Si no está completamente satisfecho con nuestro producto, envíe por correo una copia del recibo y el producto restante a la dirección que figura a continuación y llámenos al 1800 Labisan (522-4726).
Distribuido para Lupuca Pharma GmbH por Labisan Americas, LLC. Norwalk, CT 06851. Hecho en Austria.
LOT221417 A Artículo # 71625 CAD 11/2019
Labisan es una marca registrada de Lupuca Pharma Gmbh., Y Labisan Americas, LLC.
Todas las marcas comerciales y derechos de autor son propiedad de Lupuca Pharma GmbH. y licenciado a Labisan Americas, LLC., grupo de empresas.
Distribuido para Lupuca Pharma GmbH., Por su Distribuidor Autorizado Exclusivo, Labisan Americas, LLC. (EE. UU., Canadá, Centro y Sudamérica), Norwalk, Connecticut 06851, Hecho en Austria desde 1931.
Si tiene interés en llevar alguno de nuestros productos Labisan Lip Care, contáctenos en LabisanAmericas@gmail.com, Attn .: New Sales.

Use Topical

Uses

For treatment of cold sores/fever blisters on the lips or nose.

Temporarily relieves the symptoms of itching and pain associated with cold sores/fever blisters.

Prevents outbreak of cold sore/fever blister if applied at first indication of an outbreak (tingle, or burning sensation).